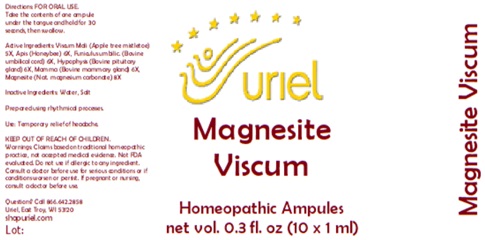 DRUG LABEL: Magnesite Viscum
NDC: 48951-7217 | Form: LIQUID
Manufacturer: Uriel Pharmacy Inc.
Category: homeopathic | Type: HUMAN OTC DRUG LABEL
Date: 20250430

ACTIVE INGREDIENTS: VISCUM ALBUM FRUITING TOP 5 [hp_X]/1 mL; APIS MELLIFERA 6 [hp_X]/1 mL; SUS SCROFA UMBILICAL CORD 6 [hp_X]/1 mL; BOS TAURUS PITUITARY GLAND 6 [hp_X]/1 mL; BOS TAURUS MAMMARY GLAND 6 [hp_X]/1 mL; MAGNESITE 8 [hp_X]/1 mL
INACTIVE INGREDIENTS: WATER; SODIUM CHLORIDE

Magnesite Viscum

INDICATIONS AND USAGE

Directions: FOR ORAL USE.

DOSAGE AND ADMINISTRATION

Take the contents of one ampule under the tongue and hold for 30 seconds, then swallow.

ACTIVE INGREDIENT

Active Ingredients: Viscum Mali (Apple tree mistletoe) 5X, Apis (Honeybee) 6X, Funiculus umbilic. (Bovine umbilical cord) 6X, Hypophysis (Bovine pituitary gland) 6X, Mamma (Bovine mammary gland) 6X, Magnesite (Nat. magnesium carbonate) 8X

Inactive Ingredients: Water, Salt

Prepared using rhythmical processes.

PURPOSE

Use: Temporary relief of headache.

KEEP OUT OF REACH OF CHILDREN.

WARNINGS

Warnings: Claims based on traditional homeopathic practice, not accepted medical evidence. Not FDA evaluated. Do not use if allergic to any ingredient. Consult a doctor before use for serious conditions or if conditions worsen or persist. If pregnant or nursing, consult a doctor before use.

QUESTIONS

Questions? Call 866.642.2858 Uriel, East Troy, WI 53120 www.urielpharmacy.com